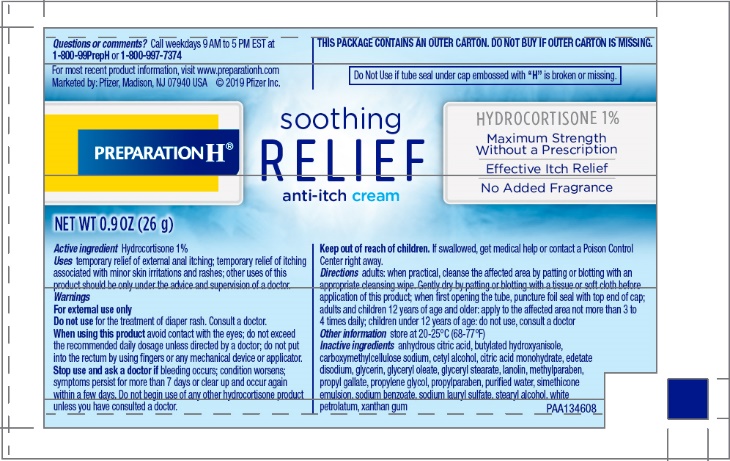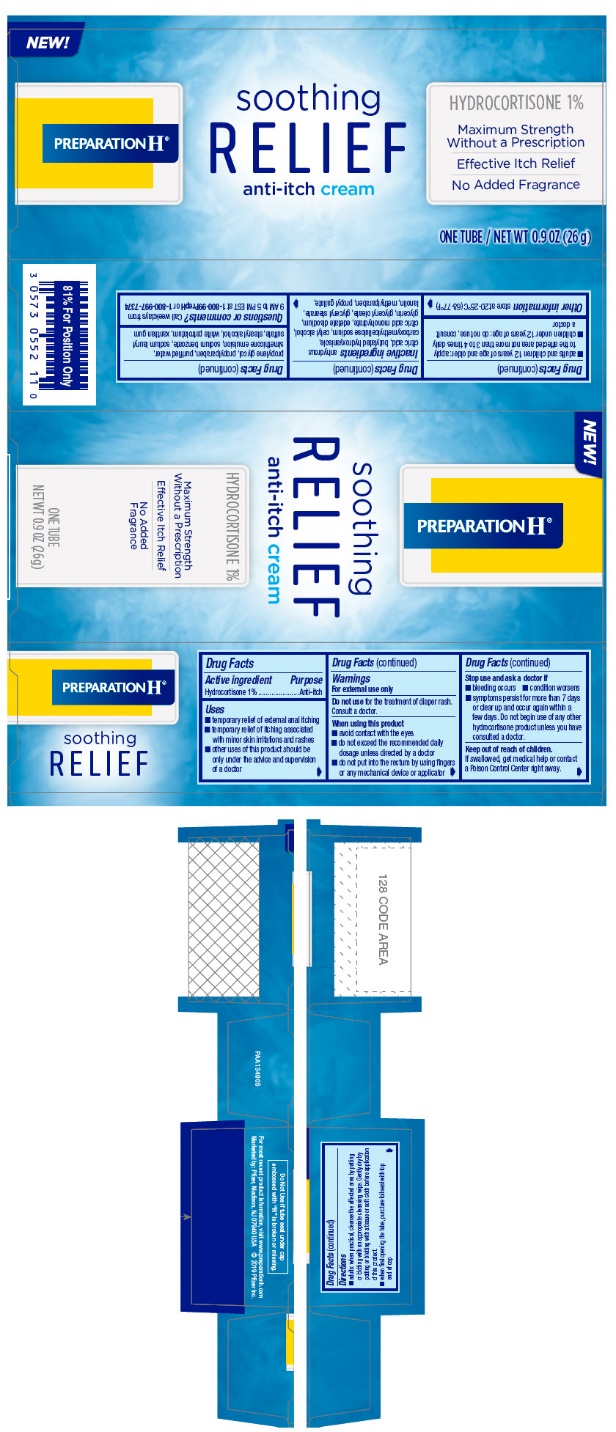 DRUG LABEL: PREPARATION H SOOTHING RELIEF ANTI-ITCH
NDC: 0573-0552 | Form: CREAM
Manufacturer: Haleon US Holdings LLC
Category: otc | Type: HUMAN OTC DRUG LABEL
Date: 20250707

ACTIVE INGREDIENTS: HYDROCORTISONE 10 mg/1 g
INACTIVE INGREDIENTS: ANHYDROUS CITRIC ACID; BUTYLATED HYDROXYANISOLE; CARBOXYMETHYLCELLULOSE SODIUM, UNSPECIFIED; CETYL ALCOHOL; CITRIC ACID MONOHYDRATE; EDETATE DISODIUM; GLYCERIN; GLYCERYL OLEATE; GLYCERYL MONOSTEARATE; LANOLIN; METHYLPARABEN; PROPYL GALLATE; PROPYLENE GLYCOL; PROPYLPARABEN; WATER; DIMETHICONE 350; SODIUM BENZOATE; SODIUM LAURYL SULFATE; STEARYL ALCOHOL; PETROLATUM; XANTHAN GUM

Drug Facts

Active ingredient

Hydrocortisone 1%

Purpose

Anti-itch

Uses

- temporary relief of external anal itching
- temporary relief of itching associated with minor skin irritations and rashes
- other uses of this product should be only under the advice and supervision of a doctor

Warnings

For external use only

DO NOT USE

Do not usefor the treatment of diaper rash. Consult a doctor.

When using this product

- avoid contact with the eyes
- do not exceed the recommended daily dosage unless directed by a doctor
- do not put into the rectum by using fingers or any mechanical device or applicator

Stop use and ask a doctor if

- bleeding occurs
- condition worsens
- symptoms persist for more than 7 days or clear up and occur again within a few days. Do not begin use of any other hydrocortisone product unless you have consulted a doctor.

Keep out of reach of children.

If swallowed, get medical help or contact a Poison Control Center right away.

Directions

- adults: when practical, cleanse the affected area by patting or blotting with an appropriate cleansing wipe. Gently dry by patting or blotting with a tissue or soft cloth before application of this product.
- when first opening the tube, puncture foil seal with top end of cap
- adults and children 12 years of age and older: apply to the affected area not more than 3 to 4 times daily
- children under 12 years of age: do not use, consult a doctor

Other information

store at 20–25°C (68–77°F)

Inactive ingredients

anhydrous citric acid, butylated hydroxyanisole, carboxymethylcellulose sodium, cetyl alcohol, citric acid monohydrate, edetate disodium, glycerin, glyceryl oleate, glyceryl stearate, lanolin, methylparaben, propyl gallate, propylene glycol, propylparaben, purified water, simethicone emulsion, sodium benzoate, sodium lauryl sulfate, stearyl alcohol, white petrolatum, xanthan gum

Questions or comments?

Call weekdays from 9 AM to 5 PM EST at 1-800-99PrepHor 1-800-997-7374

PRINCIPAL DISPLAY PANEL - 26 g Tube Label

PREPARATION H®

soothing
RELIEF
anti-itch cream

HYDROCORTISONE 1%

Maximum Strength
Without a Prescription

Effective Itch Relief

No Added Fragrance

NET WT 0.9 OZ (26 g)

PRINCIPAL DISPLAY PANEL - 26 g Tube Carton

NEW!

PREPARATION H®

soothing
RELIEF
anti-itch cream

HYDROCORTISONE 1%

Maximum Strength
Without a Prescription

Effective Itch Relief

No Added Fragrance

ONE TUBE / NET WT 0.9 0Z (26 g)